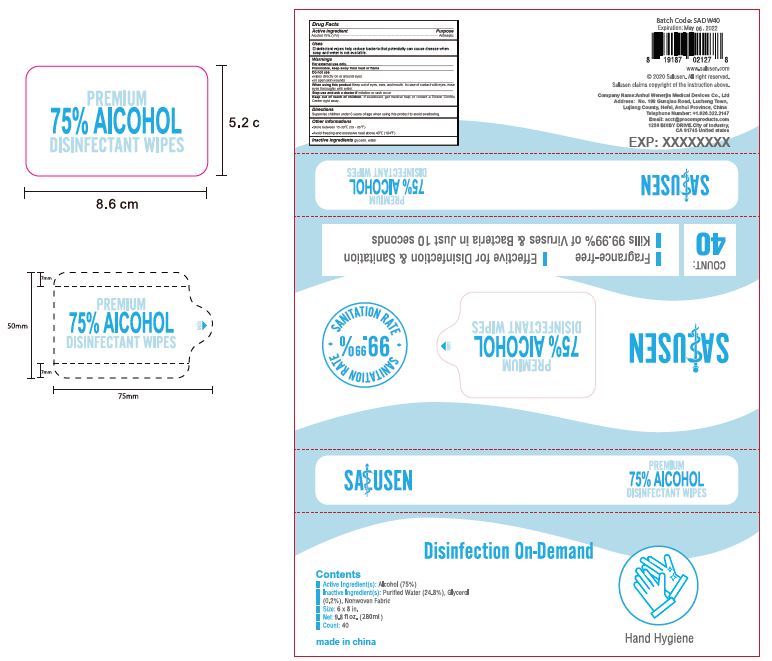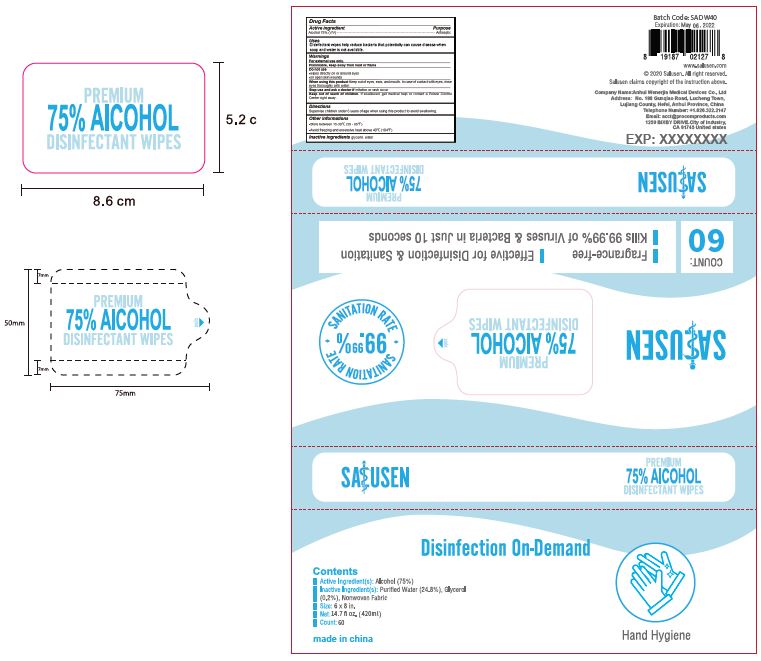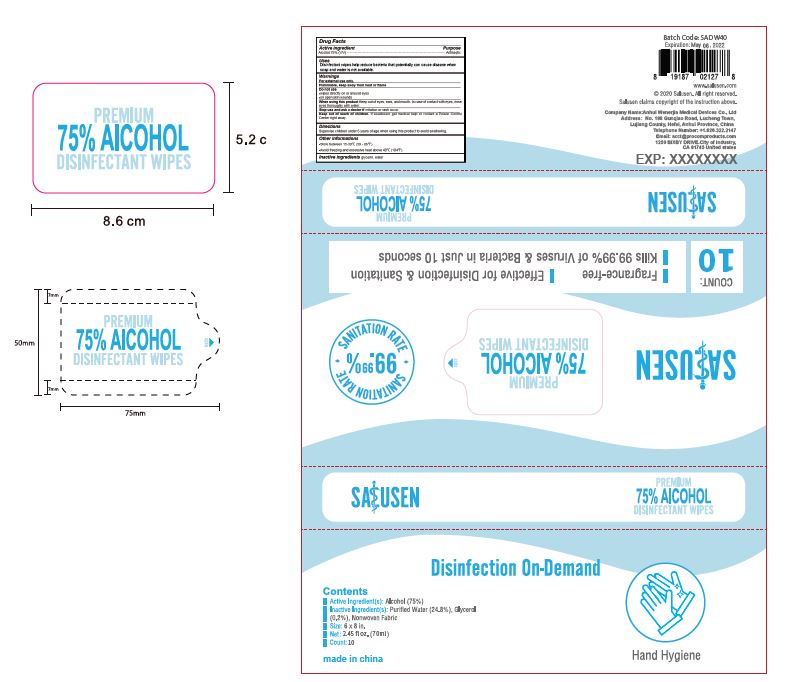 DRUG LABEL: Salusen premium 75% Disinfectant wipes
NDC: 79570-001 | Form: LIQUID
Manufacturer: Anhui Wenerjia Medical Devices Co., Ltd
Category: otc | Type: HUMAN OTC DRUG LABEL
Date: 20200727

ACTIVE INGREDIENTS: ALCOHOL 75 mL/100 mL
INACTIVE INGREDIENTS: GLYCERIN; WATER

Active Ingredient

Alcohol 75% (V/V)

Purpose

Antiseptic

Uses

Premium 75% Alcohol Disinfectant Wipes is effective for disinfection and sanitation, able to kill 99.99% of viruses and bacteria in just 10 seconds.

Warnings

For external use only.

Flammable, keep away from heat or flame.

Do not use

- wipes directly on or around eyes
- on open skin wounds

When using this product

Keep out of eyes, ears, and mouth. In case of contact with eyes, rinse eyes thoroughly with water.

Stop use and ask a doctor if irritation or rash occur.

Keep out of reach of children. If swallowed, get medical help or contact a Poison Control Center right away.

Directions

Supervise children under 6 years of age when using this product to avoid swallowing.

Other informations

- Store between 15-30oC (59-86oF)
- Avoid freezing and excessive heat above 40oC (104oF)

Inactive Ingredients

glycerine, water

Package Label/Principal Display Panel

Salusen Alcohol Wipes 10 pcs (70 ml)

NDC 79570-001-01

Salusen Alcohol Wipes 40 pcs (280 ml)

NDC 79570-001-02

Salusen Alcohol Wipes 60 pcs (420 ml)

NDC 79570-001-03